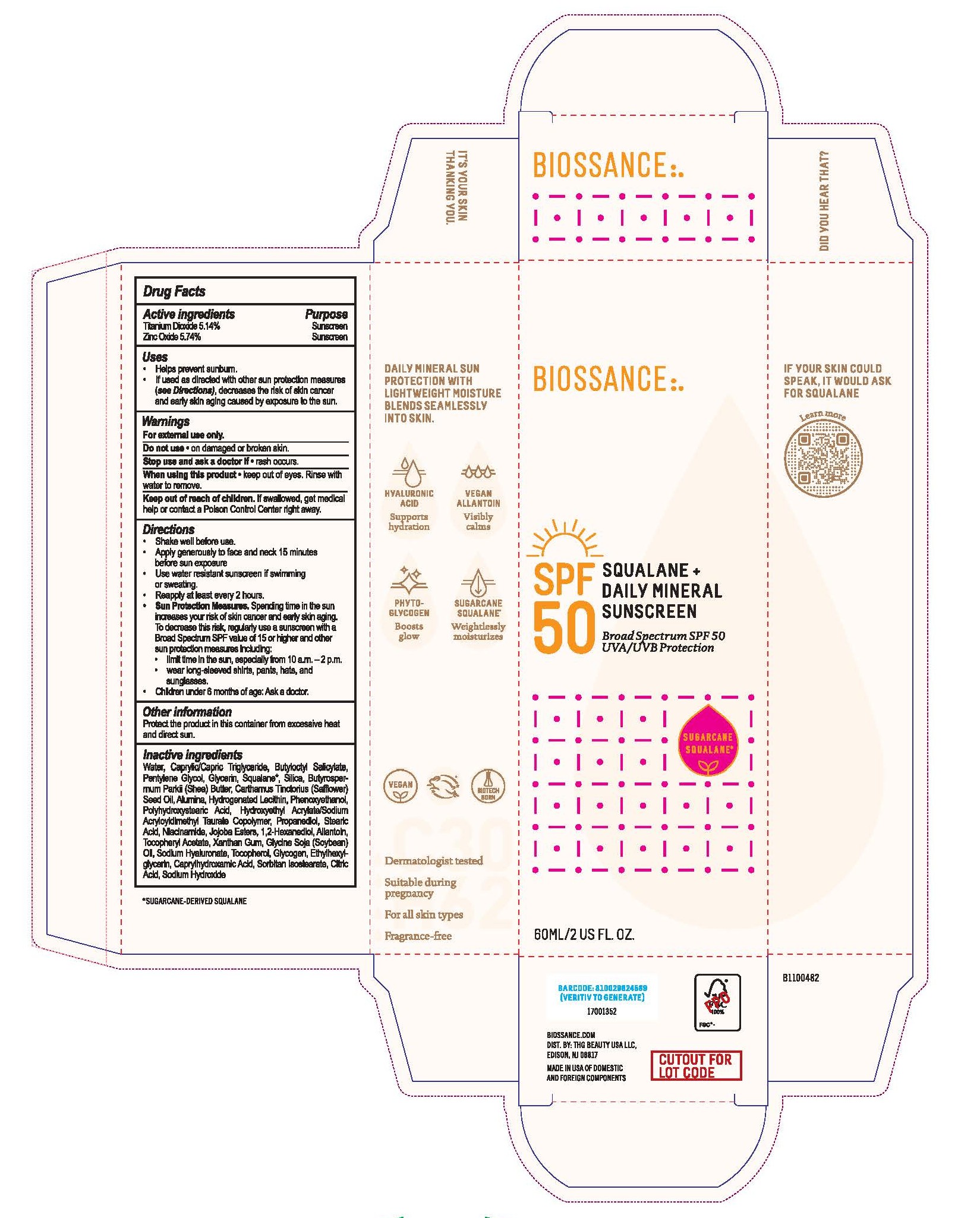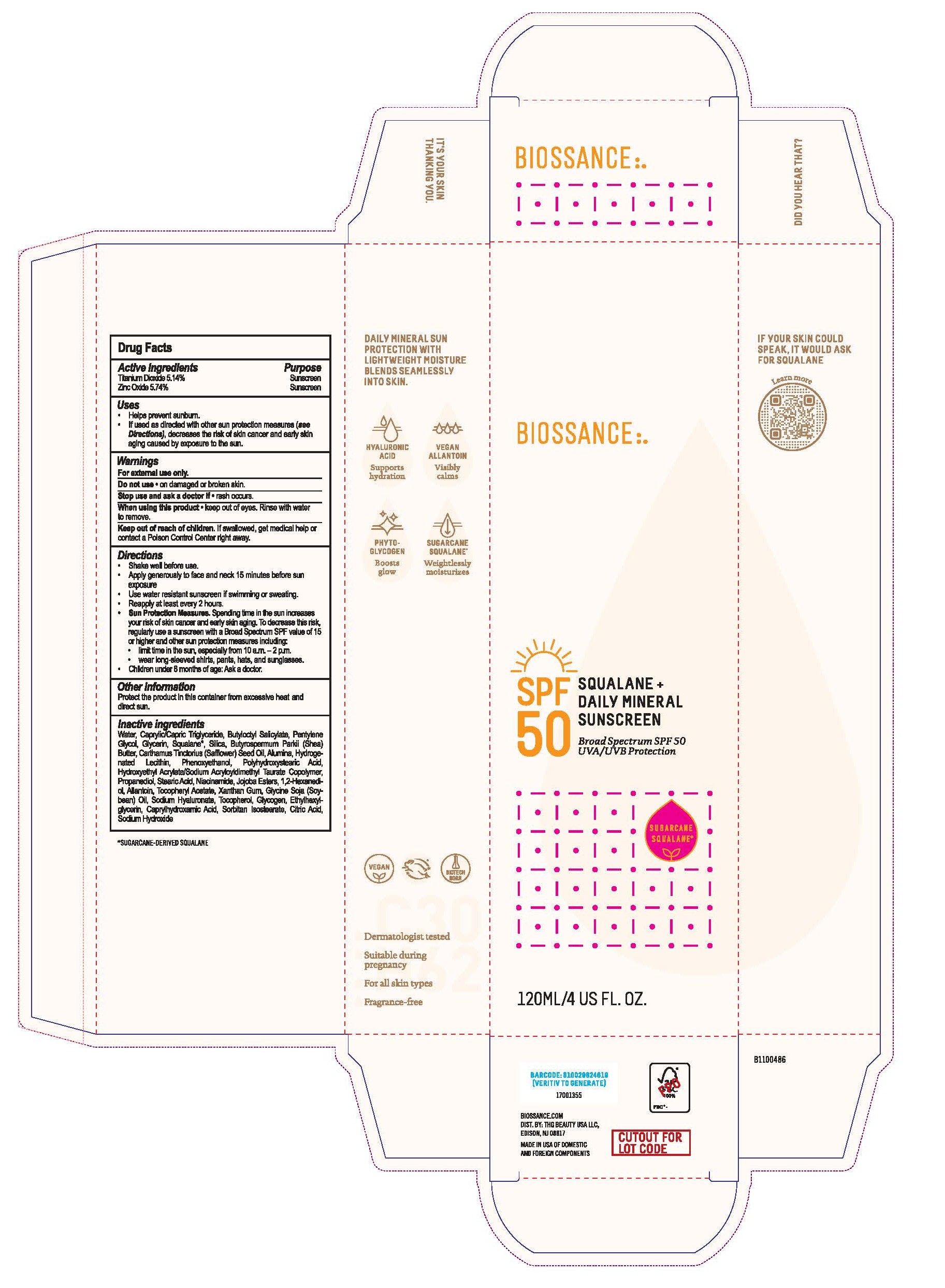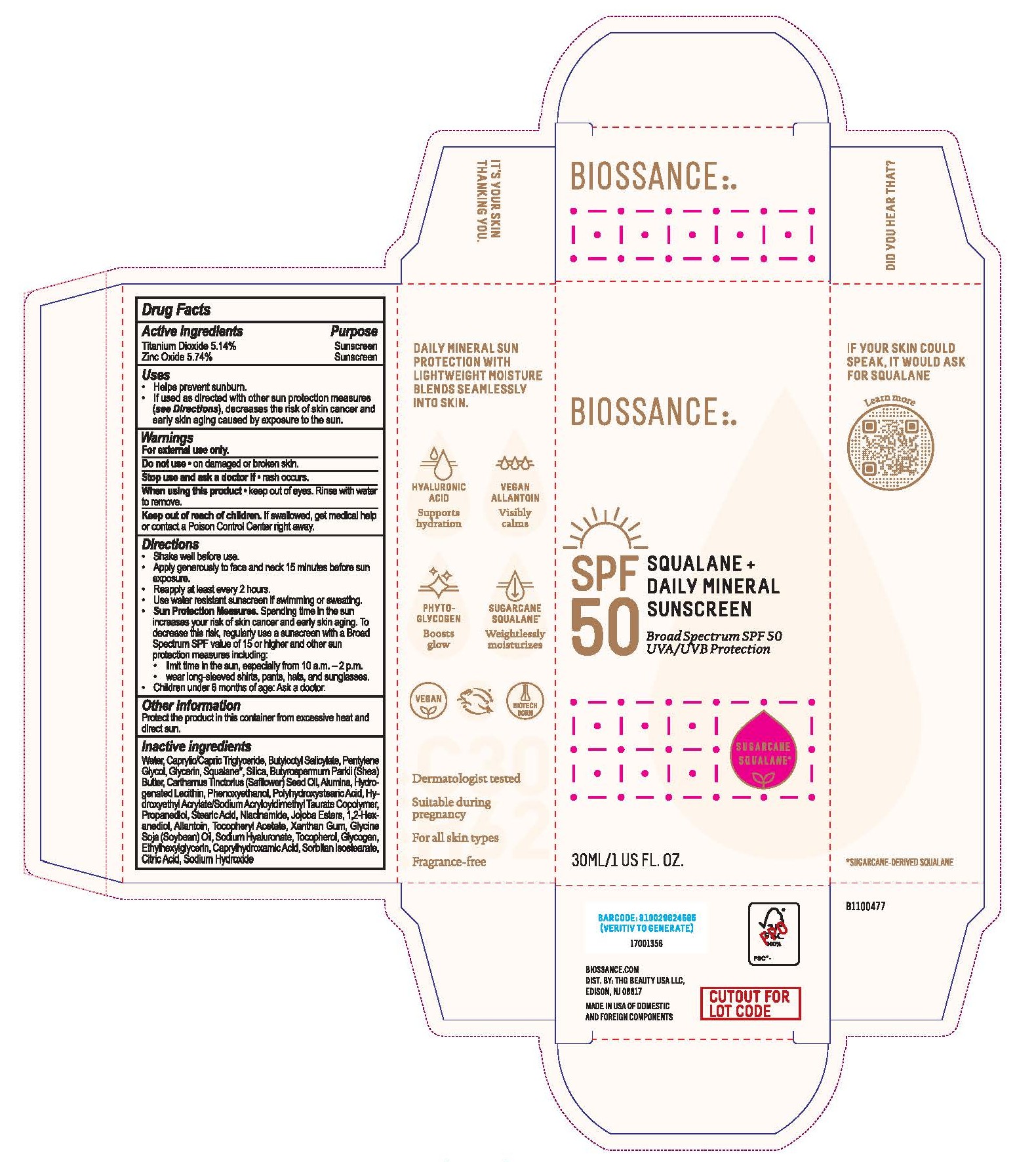 DRUG LABEL: Biossance Squalane and Daily Mineral Sunscreen Broad Spectrum SPF 50
NDC: 84448-801 | Form: CREAM
Manufacturer: THG Beauty USA LLC
Category: otc | Type: HUMAN OTC DRUG LABEL
Date: 20251127

ACTIVE INGREDIENTS: ZINC OXIDE 5.74 g/100 mL; TITANIUM DIOXIDE 5.1359 g/100 mL
INACTIVE INGREDIENTS: PROPANEDIOL; NIACINAMIDE; HYDROGENATED SOYBEAN LECITHIN; ALUMINA; SILICA; CAPRYLHYDROXAMIC ACID; CAPRYLIC/CAPRIC TRIGLYCERIDE; PENTYLENE GLYCOL; BUTYROSPERMUM PARKII (SHEA) BUTTER; GLYCERIN; SODIUM HYDROXIDE; WATER; JOJOBA OIL, RANDOMIZED; 1,2-HEXANEDIOL; ALPHA-TOCOPHEROL ACETATE; BUTYLOCTYL SALICYLATE; SQUALANE; PHENOXYETHANOL; POLYHYDROXYSTEARIC ACID (2300 MW); HYDROXYETHYL ACRYLATE/SODIUM ACRYLOYLDIMETHYL TAURATE COPOLYMER (45000 MPA.S AT 1%); STEARIC ACID; CARTHAMUS TINCTORIUS (SAFFLOWER) SEED OIL; ALLANTOIN; XANTHAN GUM; SOYBEAN OIL; SODIUM HYALURONATE; TOCOPHEROL; GLYCOGEN; ETHYLHEXYLGLYCERIN; SORBITAN ISOSTEARATE; CITRIC ACID

ACTIVE INGREDIENT

Titanium Dioxide 5.14%

Zinc Oxide 5.74%

PURPOSE

Sunscreen

INDICATIONS AND USAGE

- Helps prevent sunburn.
- If used as directed with other sun protection measures (see Directions), decreases the risk of skin cancer and early skin aging caused by exposure to the sun.

WARNINGS

For external use only.

Do not use on damaged or broken skin.

Stop use and ask a doctor if rash occurs.

When using this product keep out of eyes. Rinse with water to remove.

Keep out of reach of children. If swallowed, get medical help or contact a Poison Control Centre right away.

DOSAGE AND ADMINISTRATION

- Shake well before use.
- Apply generously to face and neck 15 minutes before sun exposure.
- Use water resistant sunscreen if swimming or sweating.
- Reapply at least every 2 hours.
- Sun Protection Measures. Spending time in the sun increases your risk of skin cancer and early skin aging. To decrease this risk, regularly use a sunscreen with Broad Spectrum SPF value of 15 or higher and other sun protection measures including:

- limit time in the sun, especially from 10 a.m. - 2 p.m.

- wear long-sleeved shirts, pants, hats, and sunglasses.

- Children under 6 months of age: Ask a doctor.

OTHER SAFETY INFORMATION

Protect the product in this container from excessive heat and direct sun.

INACTIVE INGREDIENT

WATER, CAPRYLIC/CAPRIC TRIGLYCERIDE, BUTYLOCTYL SALICYLATE, PENTYLENE GLYCOL, GLYCERIN, SQUALANE, SILICA, BUTYROSPERMUM PARKII (SHEA) BUTTER, CARTHAMUS TINCTORIUS (SAFFLOWER) SEED OIL, ALUMINA, HYDROGENATED LECITHIN, PHENOXYETHANOL, POLYHYDROXYSTEARIC ACID, HYDROXYETHYL ACRYLATE/SODIUM ACRYLOYLDIMETHYL TAURATE COPOLYMER, PROPANEDIOL, STEARIC ACID, NIACINAMIDE, JOJOBA ESTERS, 1,2-HEXANEDIOL, ALLANTOIN, TOCOPHERYL ACETATE, XANTHAN GUM, GLYCINE SOJA (SOYBEAN) OIL, SODIUM HYALURONATE, TOCOPHEROL, GLYCOGEN, ETHYLHEXYLGLYCERIN, CAPRYLHYDROXAMIC ACID, SORBITAN ISOSTEARATE, CITRIC ACID, SODIUM HYDROXIDE